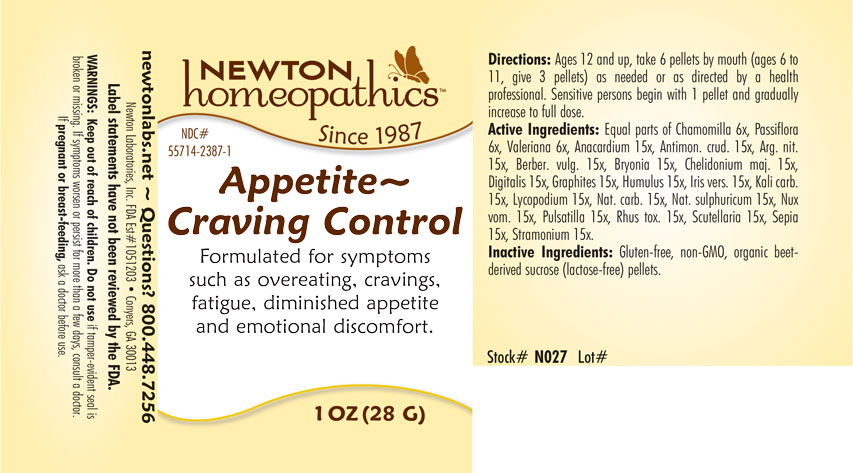 DRUG LABEL: Appetite - Craving Control
NDC: 55714-2387 | Form: PELLET
Manufacturer: Newton Laboratories, Inc.
Category: homeopathic | Type: HUMAN OTC DRUG LABEL
Date: 20250206

ACTIVE INGREDIENTS: SEMECARPUS ANACARDIUM JUICE 15 [hp_X]/1 g; ANTIMONY TRISULFIDE 15 [hp_X]/1 g; SILVER NITRATE 15 [hp_X]/1 g; BERBERIS VULGARIS ROOT BARK 15 [hp_X]/1 g; BRYONIA ALBA ROOT 15 [hp_X]/1 g; CHELIDONIUM MAJUS 15 [hp_X]/1 g; DIGITALIS 15 [hp_X]/1 g; GRAPHITE 15 [hp_X]/1 g; HOPS 15 [hp_X]/1 g; IRIS VERSICOLOR ROOT 15 [hp_X]/1 g; POTASSIUM CARBONATE 15 [hp_X]/1 g; LYCOPODIUM CLAVATUM SPORE 15 [hp_X]/1 g; SODIUM CARBONATE 15 [hp_X]/1 g; SODIUM SULFATE 15 [hp_X]/1 g; STRYCHNOS NUX-VOMICA SEED 15 [hp_X]/1 g; PULSATILLA VULGARIS 15 [hp_X]/1 g; TOXICODENDRON PUBESCENS LEAF 15 [hp_X]/1 g; SCUTELLARIA LATERIFLORA 15 [hp_X]/1 g; SEPIA OFFICINALIS JUICE 15 [hp_X]/1 g; DATURA STRAMONIUM 15 [hp_X]/1 g; MATRICARIA RECUTITA 6 [hp_X]/1 g; PASSIFLORA INCARNATA FLOWERING TOP 6 [hp_X]/1 g; VALERIAN 6 [hp_X]/1 g
INACTIVE INGREDIENTS: SUCROSE

Appetite 2387P

INDICATIONS & USAGE SECTION

Formulated for symptoms such as overeating, cravings, fatigue, diminished appetite and emotional discomfort.

DOSAGE & ADMINISTRATION SECTION

Directions: Ages 12 and up, take 6 pellets orally (ages 6 to 11, give 3 pellets) as needed or as directed by a health professional. Sensitive persons begin with 1 pellet and gradually increase to full dose.

OTC - ACTIVE INGREDIENT SECTION

Equal parts of Chamomilla 6x, Passiflora incarnata 6x, Valeriana officinalis 6x, Anacardium orientale 15x, Antimonium crudum 15x, Argentum nitricum 15x, Berberis vulgaris 15x, Bryonia 15x, Chelidonium majus 15x, Digitalis purpurea 15x, Graphites 15x, Humulus lupulus 15x, Iris versicolor 15x, Kali carbonicum 15x, Lycopodium clavatum 15x, Natrum carbonicum 15x, Natrum sulphuricum 15x, Nux vomica 15x, Pulsatilla 15x, Rhus toxicodendron 15x, Scutellaria lateriflora 15x, Sepia 15x, Stramonium 15x.

OTC - PURPOSE SECTION

Formulated for symptoms such as overeating, cravings, fatigue, diminished appetite and emotional discomfort.

INACTIVE INGREDIENT SECTION

Inactive Ingredients: Gluten-free, non-GMO, organic beet-derived sucrose (lactose-free) pellets.

QUESTIONS SECTION

newtonlabs.net – Questions? 800.448.7256

Newton Laboratories, Inc. FDA Est # 1051203 - Conyers, GA 30013

WARNINGS SECTION

WARNINGS: Keep out of reach of children. Do not use if tamper-evident seal is broken or missing. If symptoms worsen or persist for more than a few days, consult a doctor. If pregnant or breast-feeding, ask a doctor before use.

OTC - PREGNANCY OR BREAST FEEDING SECTION

If pregnant or breast-feeding, ask a doctor before use.

OTC - KEEP OUT OF REACH OF CHILDREN SECTION

Keep out of reach of children.